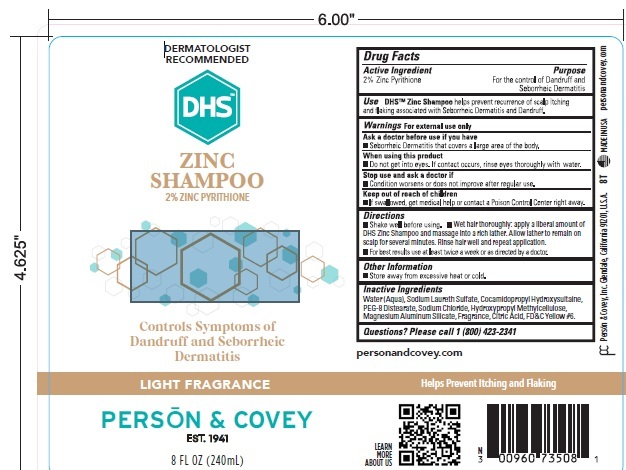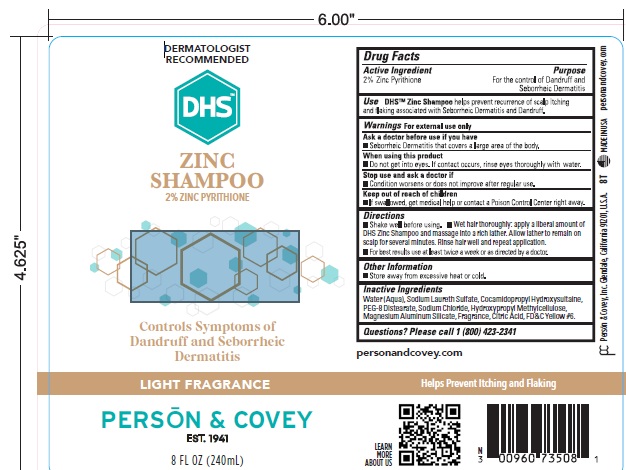 DRUG LABEL: DHS ZINC
NDC: 0096-0735 | Form: SHAMPOO
Manufacturer: Person and Covey
Category: otc | Type: HUMAN OTC DRUG LABEL
Date: 20251125

ACTIVE INGREDIENTS: PYRITHIONE ZINC 20 mg/1 mL
INACTIVE INGREDIENTS: WATER; COCAMIDOPROPYL HYDROXYSULTAINE; SODIUM CHLORIDE; PEG-8 DISTEARATE; HYPROMELLOSES; MAGNESIUM ALUMINUM SILICATE; FD&C YELLOW NO. 6; TRIETHANOLAMINE LAURYL SULFATE

DHS ZINC

WARNINGS AND PRECAUTIONS

For external use only. Ask a physician before use if you have Psoriasis or Seborrheic Dermatitis that covers a large area of the body. Do not get into eyes. If contact occurs, rinse eyes thoroughly with water. Stop use and ask a physician if condition worsens or does not improve after regular use.

Dosage and Administration

Shake well before using. Wet hair thoroughly. Apply a liberal amount of shampoo and massage into a rich lather. Allow lather to remain on scalp for several minutes. Rinse hair well and repeat application. For best results use at least twice a week or as directed by a physician.

Indications and Use

Helps prevent recurrence of scalp itching and flaking associated with Seborrheic Dermatitis and Dandruff.

OTC - KEEP OUT OF REACH OF CHILDREN

Yes. If swallowed, get medical help or contact a Poison Control Center right away.

PURPOSE

Recommended for control of Dandruff of Seborrheic Dermatitis

INACTIVE INGREDIENTS

Purified Water

TEA Lauryl Sulfate

Cocamidopropyl Hydroxysultaine

Sodium Chloride

PEG 8 Distearate

Methocel E4M Premium

Veegum

Herbal Bouquet No. 1751 Perfume

FD&C Yellow No.6

Active Ingredient

pyrithione zinc